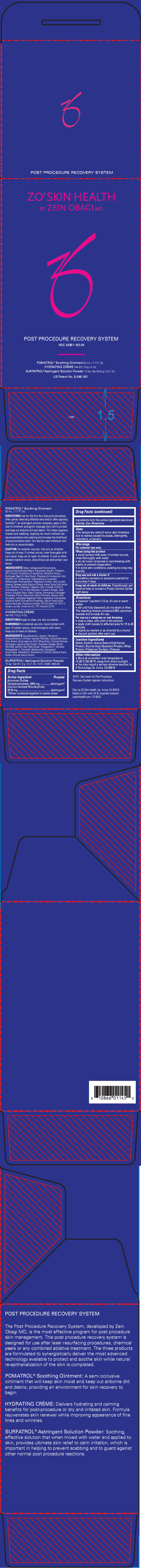 DRUG LABEL: ZO Skin Health Post Procedure Recovery System
NDC: 42851-193 | Form: KIT | Route: TOPICAL
Manufacturer: ZO Skin Health, Inc.
Category: otc | Type: HUMAN OTC DRUG LABEL
Date: 20241227

ACTIVE INGREDIENTS: ALUMINUM ACETATE 4866 mg/6 g
INACTIVE INGREDIENTS: WATER; OAT; SOY PROTEIN; WHEY; POTASSIUM SORBATE

ZO®Skin Health Post Procedure Recovery System

Drug Facts

ACTIVE INGREDIENT

Active Ingredient | Purpose
Aluminum Sulfate Tetradecahydrate, 2850 mg | Astringent [When combined together in water, these ingredients form the active ingredient aluminum acetate. See Directions]
Calcium Acetate Monohydrate, 2016 mg | Astringent

Uses

- For temporary relief of minor skin irritations due to rashes caused by soaps, detergents, cosmetics, or jewelry.

Warnings

For external use only.

When using this product

- avoid contact with eyes. If contact occurs, rinse thoroughly with water.
- do not cover compress or wet dressing with plastic to prevent evaporation
- in some skin conditions, soaking too long may overdry

Stop use and ask a doctor if

- condition worsens or symptoms persist for more than 7 days

Keep out of reach of children.If swallowed, get medical help or contact a Poison Control Center right away.

Directions

- dissolve 1 packet in 12 oz. of cool or warm water.
- stir until fully dissolved; do not strain or filter.

The resulting mixture contains 0.45% aluminum acetate and is ready for use.

For use as a compress or wet dressing:

- soak a clean, soft cloth in the solution
- apply cloth loosely to affected area for 15 to 30 minutes
- repeat as needed or as directed by a doctor
- discard solution after each use

Inactive Ingredients

Water, Dextrin, Avena Sativa (Oat) Kernel Protein, Glycine Soja (Soybean) Protein, Whey Protein, Potassium Sorbate, Chitosan.

Other Information

- Store at controlled room temperature: 15-30°C (59-86°F), away from direct sunlight.
- You may report a serious adverse reaction to: 5 Technology Dr. Irvine, CA 92618

Dist. by ZO Skin Health, Inc. Irvine, CA 92618

PRINCIPAL DISPLAY PANEL - Kit Carton

ZO®SKIN HEALTH
BY ZEIN OBAGI MD

POST PROCEDURE RECOVERY SYSTEM

NDC 42851-193-06

POMATROL®Soothing Ointment 50 mL / 1.7 Fl. Oz.
HYDRATING CRÈME Net Wt.113 g / 4 Oz.
SURFATROL®Astringent Solution Powder 10 ea. Net Wt.6 g / 0.21 Oz.

US Patent No. 9,248,160